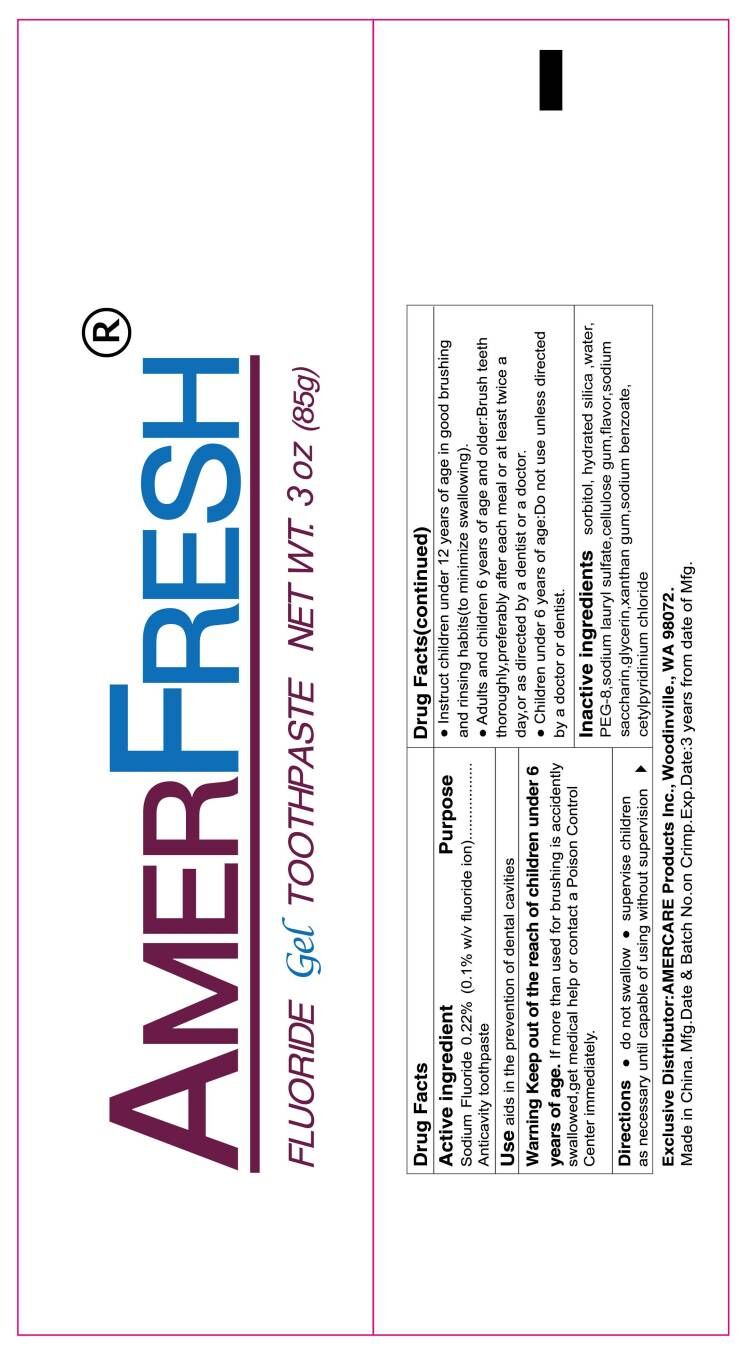 DRUG LABEL: AMERFRESH FLUORIDE gel
NDC: 85162-001 | Form: PASTE, DENTIFRICE
Manufacturer: Yangzhou ONE & ONLY Personal Care Products Co., LTD
Category: otc | Type: HUMAN OTC DRUG LABEL
Date: 20250116

ACTIVE INGREDIENTS: SODIUM FLUORIDE 0.1 g/100 g
INACTIVE INGREDIENTS: SACCHARIN SODIUM; SORBITOL; GLYCERIN; HYDRATED SILICA; SODIUM LAURYL SULFATE; XANTHAN GUM; WATER; SODIUM BENZOATE; CETYLPYRIDINIUM CHLORIDE

85162-001

Active ingredients

Sodium Fluoride 0.22% (0.1 w/v Fluoride ion)

Purpose

anticavity toothpaste

Uses

Aids in the prevention of dental cavities.

Warnings

Keep out of the reach of children under 6 years of age. If more than used for brushing is accidently swallowed,get medical help or contact a Poison Control Center immediately.

Keep out of reach of children.

Directions

- do not swallow
- supervise children as necessary until capable of useing without supervision
- instruct children under 12 years of age in good brushing and rinsing habits(to minimize swallowing).
- Adults and children 6 years of age and older:Brush teeth thoroughly,preferably after each meal or at least twice a day,or as directed by a dentist or a physician.
- Children under 6 years of age:do not use unless directed by a doctor or dentist.

INACTIVE INGREDIENT

Sorbitol, Hydrated Silica, Water, PEG-8, Sodium Lauryl Sulfate, Cellulose Gum, Flavor, Sodium Saccharin, Glycerin, anthan Gum, Sodium Benzoate, Cetylpyridinium Chloride.